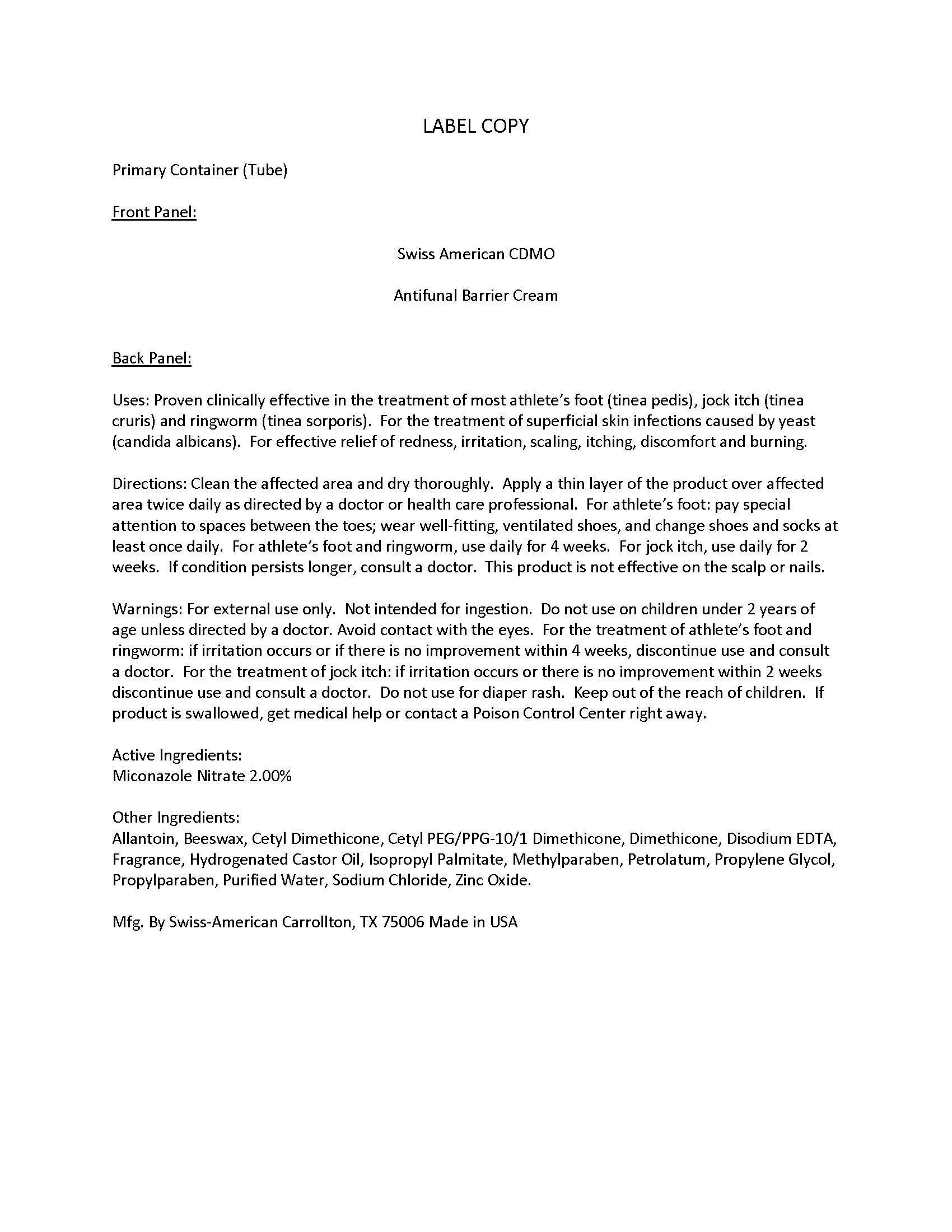 DRUG LABEL: Private Label Antifungal Barrier Cream
NDC: 60232-0009 | Form: CREAM
Manufacturer: Swiss-American CDMO, LLC
Category: otc | Type: HUMAN OTC DRUG LABEL
Date: 20260108

ACTIVE INGREDIENTS: MICONAZOLE NITRATE 20 g/1000 g
INACTIVE INGREDIENTS: WATER; ALLANTOIN; EDETATE DISODIUM; SODIUM CHLORIDE; METHYLPARABEN; PROPYLENE GLYCOL; PETROLATUM; DIMETHICONE 1000; CETYL DIMETHICONE 25; CETYL PEG/PPG-10/1 DIMETHICONE (HLB 1.5); PROPYLPARABEN; HYDROGENATED CASTOR OIL; YELLOW WAX; ZINC OXIDE; ISOPROPYL PALMITATE; CUCUMBER

Antifungal Barrier Cream

Warnings

For external use only. Not intended for ingestion. Do not use on children under 2 years of age unless directed by a doctor. Avoid contact with the eyes. For the treatment of athlete’s foot and ringworm: if irritation occurs or if there is no improvement within 4 weeks, discontinue use and consult a doctor. For the treatment of jock itch: if irritation occurs or there is no improvement within 2 weeks discontinue use and consult a doctor. Do not use for diaper rash. Keep out of the reach of children. If product is swallowed, get medical help or contact a Poison Control Center right away

Use and Directions

Proven clinically effective in the treatment of most athlete’s foot (tinea pedis), jock itch (tinea cruris) and ringworm (tinea sorporis). For the treatment of superficial skin infections caused by yeast (candida albicans). For effective relief of redness, irritation, scaling, itching, discomfort and burning.

Clean the affected area and dry thoroughly. Apply a thin layer of the product over affected area twice daily as directed by a doctor or health care professional. For athlete’s foot: pay special attention to spaces between the toes; wear well-fitting, ventilated shoes, and change shoes and socks at least once daily. For athlete’s foot and ringworm, use daily for 4 weeks. For jock itch, use daily for 2 weeks. If condition persists longer, consult a doctor. This product is not effective on the scalp or nails.

Keep out of reach of children

Active Ingredient

Miconazole Nitrate 2.00%

Inactive Ingredient

Allantoin, Beeswax, Cetyl Dimethicone, Cetyl PEG/PPG-10/1 Dimethicone, Dimethicone, Disodium EDTA, Fragrance, Hydrogenated Castor Oil, Isopropyl Palmitate, Methylparaben, Petrolatum, Propylene Glycol, Propylparaben, Purified Water, Sodium Chloride, Zinc Oxide